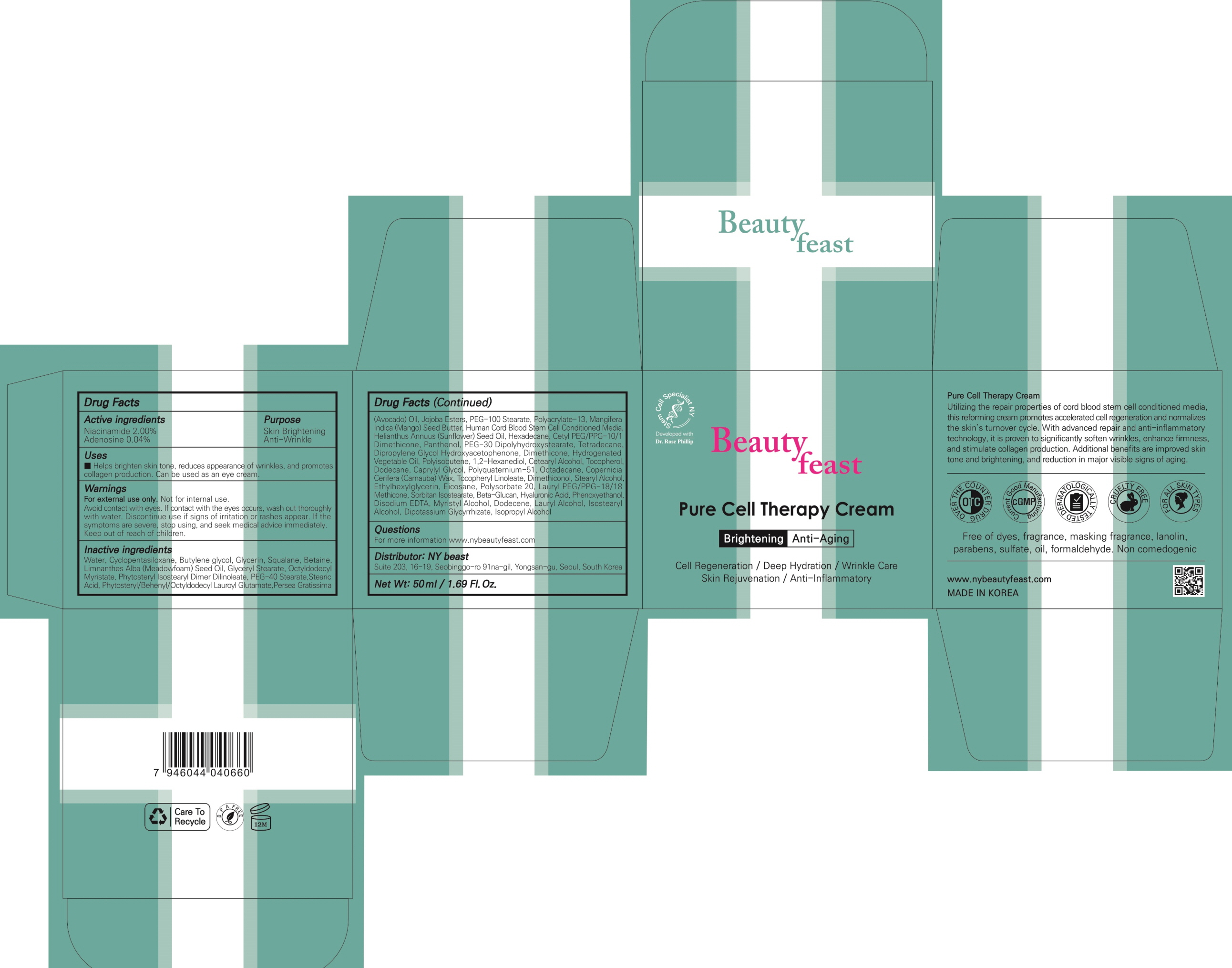 DRUG LABEL: Pure Cell Therapy
NDC: 73651-010 | Form: CREAM
Manufacturer: NY Beast
Category: otc | Type: HUMAN OTC DRUG LABEL
Date: 20200316

ACTIVE INGREDIENTS: Niacinamide 1.0 g/50 mL; Adenosine 0.02 g/50 mL
INACTIVE INGREDIENTS: Water; Butylene glycol

ACTIVE INGREDIENT

Active ingredients: Niacinamide 2.00%, Adenosine 0.04%

INACTIVE INGREDIENT

Inactive ingredients:
Water, Cyclopentasiloxane, Butylene glycol, Glycerin, Squalane, Betaine, Limnanthes Alba (Meadowfoam) Seed Oil, Glyceryl Stearate, Octyldodecyl Myristate, Phytosteryl Isostearyl Dimer Dilinoleate, PEG-40 Stearate, Stearic Acid, Phytosteryl/Behenyl/Octyldodecyl Lauroyl Glutamate, Persea Gratissima (Avocado) Oil, Jojoba Esters, PEG-100 Stearate, Polyacrylate-13, Mangifera Indica (Mango) Seed Butter, Human Cord Blood Stem Cell Conditioned Media, Helianthus Annuus (Sunflower) Seed Oil, Hexadecane, Cetyl PEG/PPG-10/1 Dimethicone, Panthenol, PEG-30 Dipolyhydroxystearate, Tetradecane, Dipropylene Glycol, Hydroxyacetophenone, Dimethicone, Hydrogenated Vegetable Oil, Polyisobutene, 1,2-Hexanediol, Cetearyl Alcohol, Tocopherol, Dodecane, Caprylyl Glycol, Polyquaternium-51, Octadecane, Copernicia Cerifera (Carnauba) Wax, Tocopheryl Linoleate, Dimethiconol, Stearyl Alcohol, Ethylhexylglycerin, Eicosane, Polysorbate 20, Lauryl PEG/PPG-18/18 Methicone, Sorbitan Isostearate, Beta-Glucan, Hyaluronic Acid, Phenoxyethanol, Disodium EDTA, Myristyl Alcohol, Dodecene, Lauryl Alcohol, Isostearyl Alcohol, Dipotassium Glycyrrhizate, Isopropyl Alcohol

PURPOSE

Purpose: Skin Brightening, Anti-Wrinkle

WARNINGS

For external use only. Not for internal use.
Avoid contact with eyes. If contact with the eyes occurs, wash out thoroughly with water. Discontinue use if signs of irritation or rashes appear. If the symptoms are severe, stop using, and seek medical advice immediately. Keep out of reach of children.

KEEP OUT OF REACH OF CHILDREN

Uses

■ Helps brighten skin tone, reduces appearance of wrinkles, and promotes collagen production. Can be used as an eye cream.

Directions

■Apply the Pure Cell Therapy Cream after cleansing face and neck. For use in the morning and at night. Massage into skin gently until thoroughly absorbed.

QUESTIONS

For more information www.nybeautyfeast.com